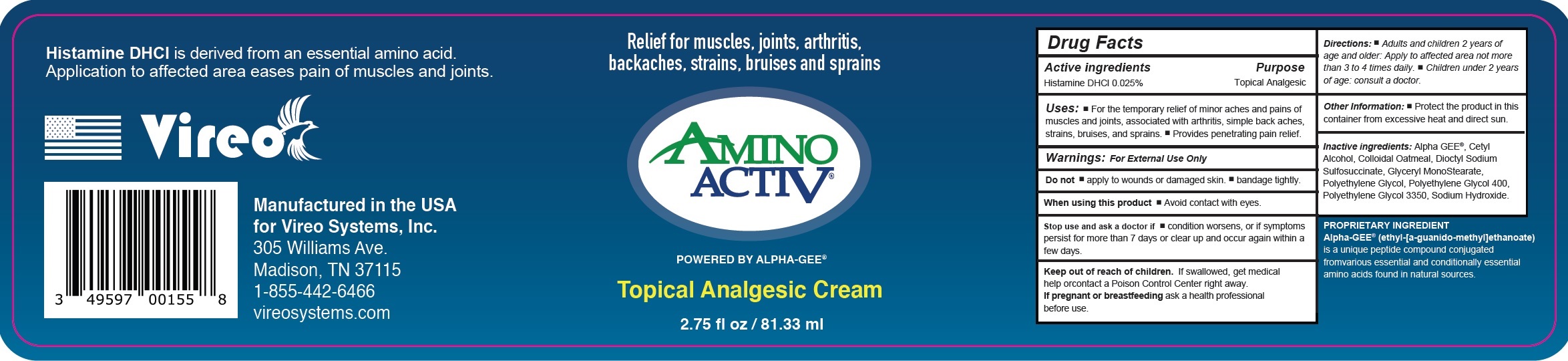 DRUG LABEL: AMINO ACTIVE Topical Analgesic Cream
NDC: 82908-357 | Form: CREAM
Manufacturer: VIREO SYSTEMS, INC.
Category: otc | Type: HUMAN OTC DRUG LABEL
Date: 20231111

ACTIVE INGREDIENTS: HISTAMINE DIHYDROCHLORIDE 0.25 mg/1 mL
INACTIVE INGREDIENTS: CETYL ALCOHOL; OATMEAL; DOCUSATE SODIUM; GLYCERYL MONOSTEARATE; POLYETHYLENE GLYCOL, UNSPECIFIED; POLYETHYLENE GLYCOL 400; POLYETHYLENE GLYCOL 3350; SODIUM HYDROXIDE

AMINO ACTIVE Topical Analgesic Cream

Active ingredients

Histamine DHCl 0.025%

Purpose

Topical Analgesic

Uses:

- For the temporary relief of minor aches and pains of muscles and joints, associated with arthritis, simple back aches, strains, bruises, and sprains.
- Provides penetrating pain relief.

Warnings:

For External Use Only

Do not

- apply to wounds or damaged skin.
- bandage tightly.

When using this product

- Avoid contact with eyes.

Stop use and ask a doctor if

- condition worsens, or if symptoms persist for more than 7 days or clear up and occur again within a few days.

Keep out of reach of children.

If swallowed, get medical help orcontact a Poison Control Center right away.

If pregnant or breastfeeding

ask a health professional before use.

Directions:

- Adults and children 2 years of age and older: Apply to affected area not more than 3 to 4 times daily.
- Children under 2 years of age: consult a doctor.

Other Information:

- Protect the product in this container from excessive heat and direct sun.

Inactive ingredients:

Alpha GEE®, Cetyl Alcohol, Colloidal Oatmeal, Dioctyl Sodium Sulfosuccinate, Glyceryl MonoStearate, Polyethylene Glycol, Polyethylene Glycol 400, Polyethylene Glycol 3350, Sodium Hydroxide.